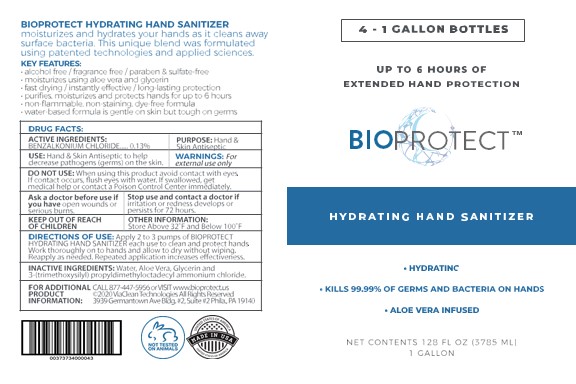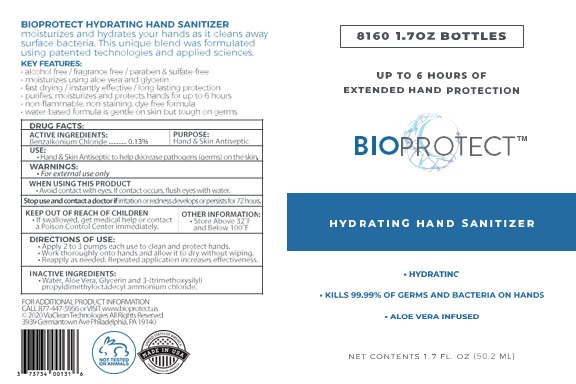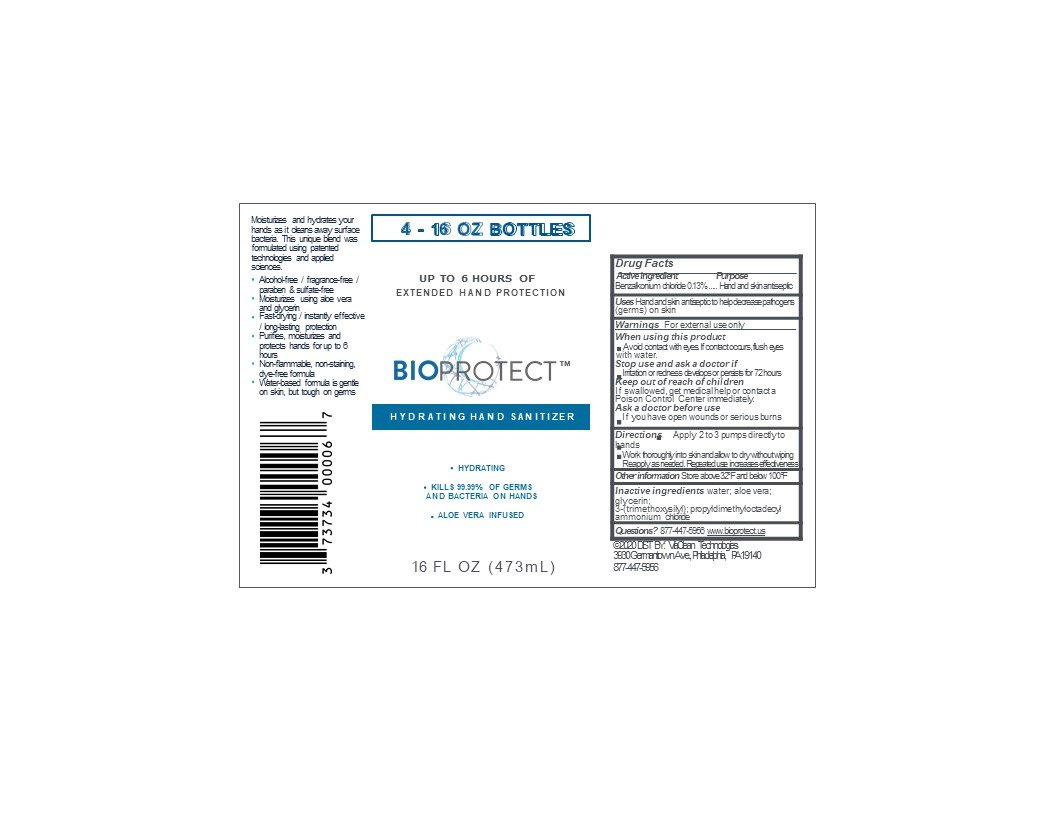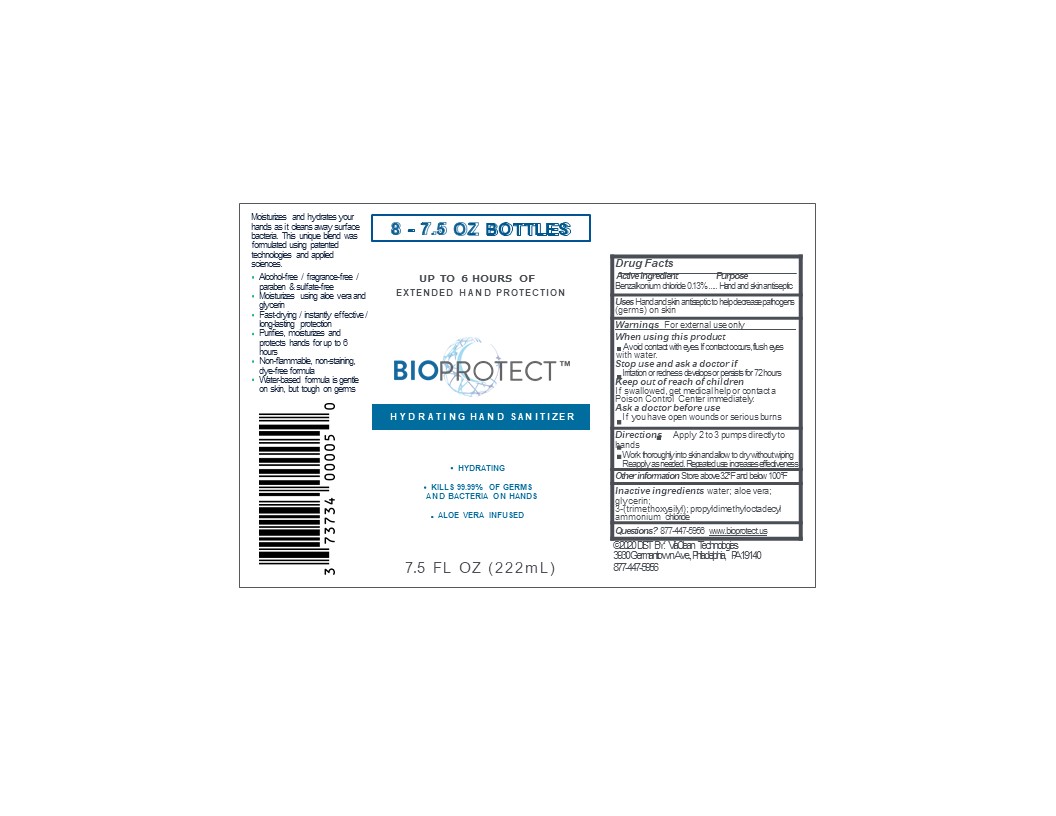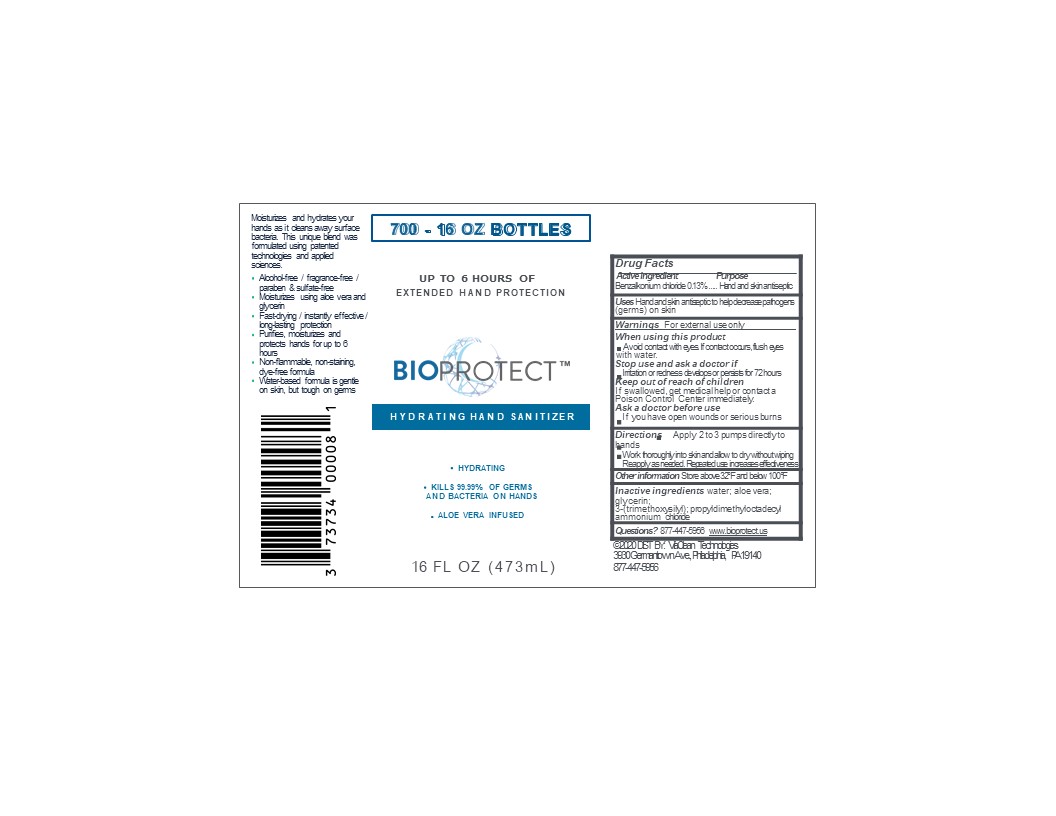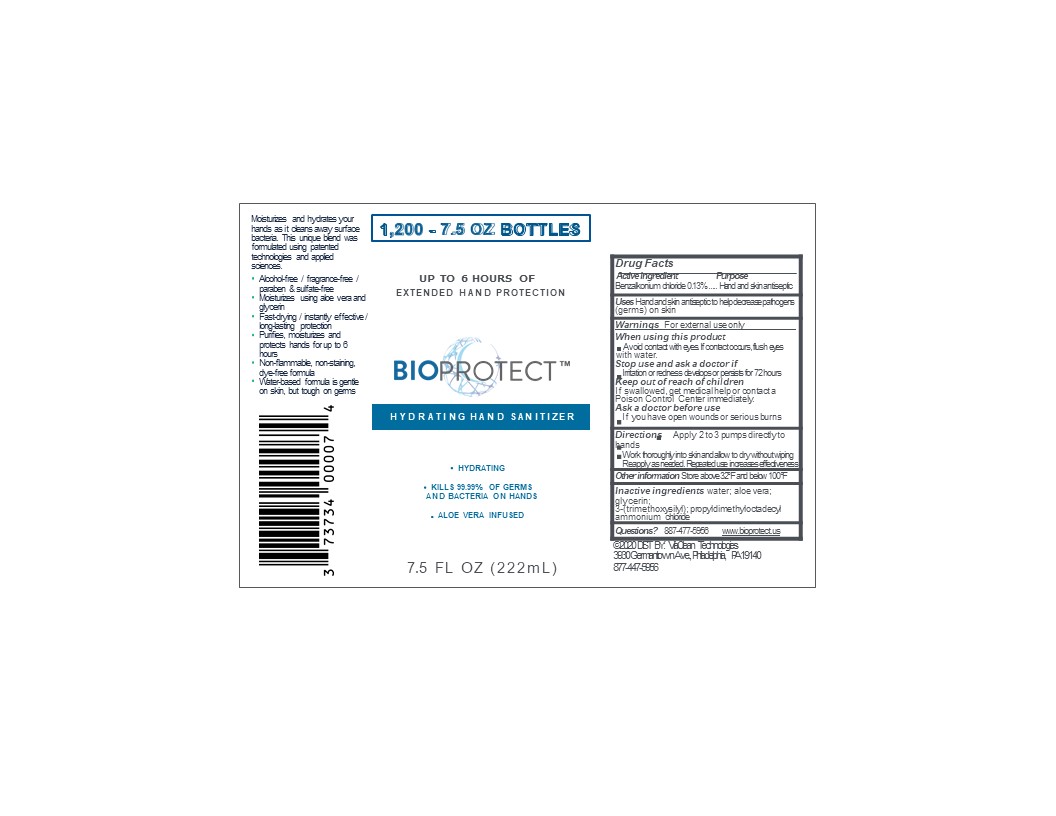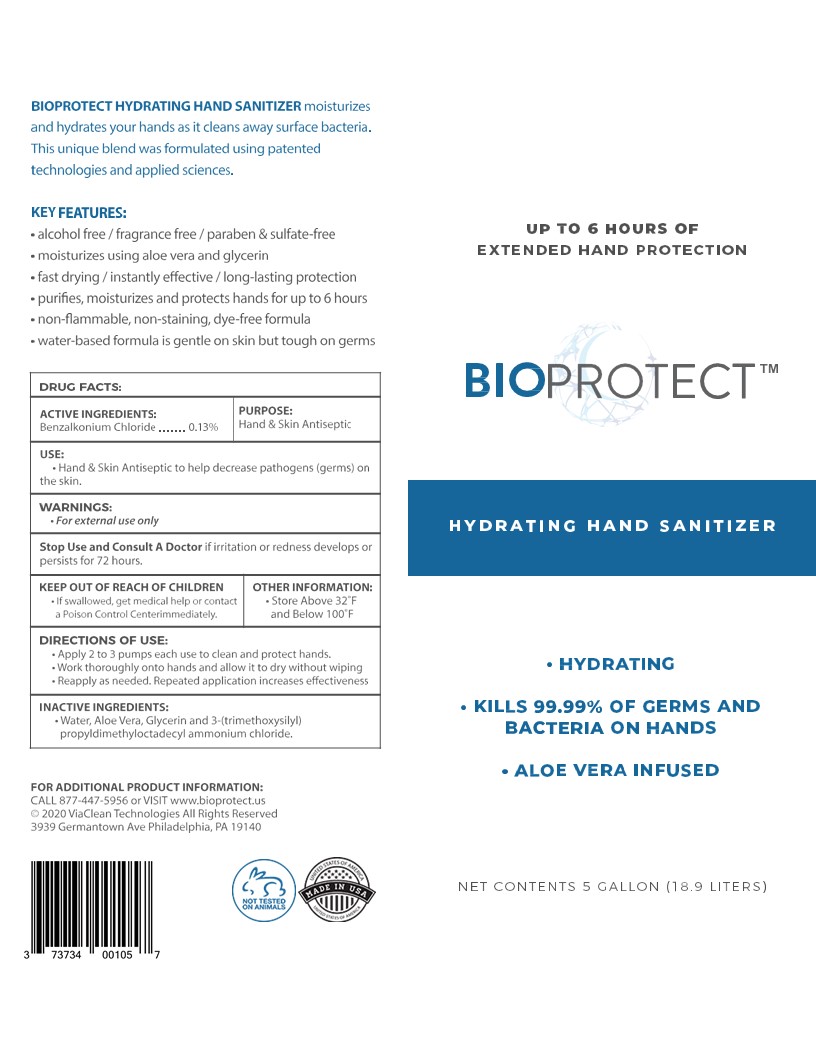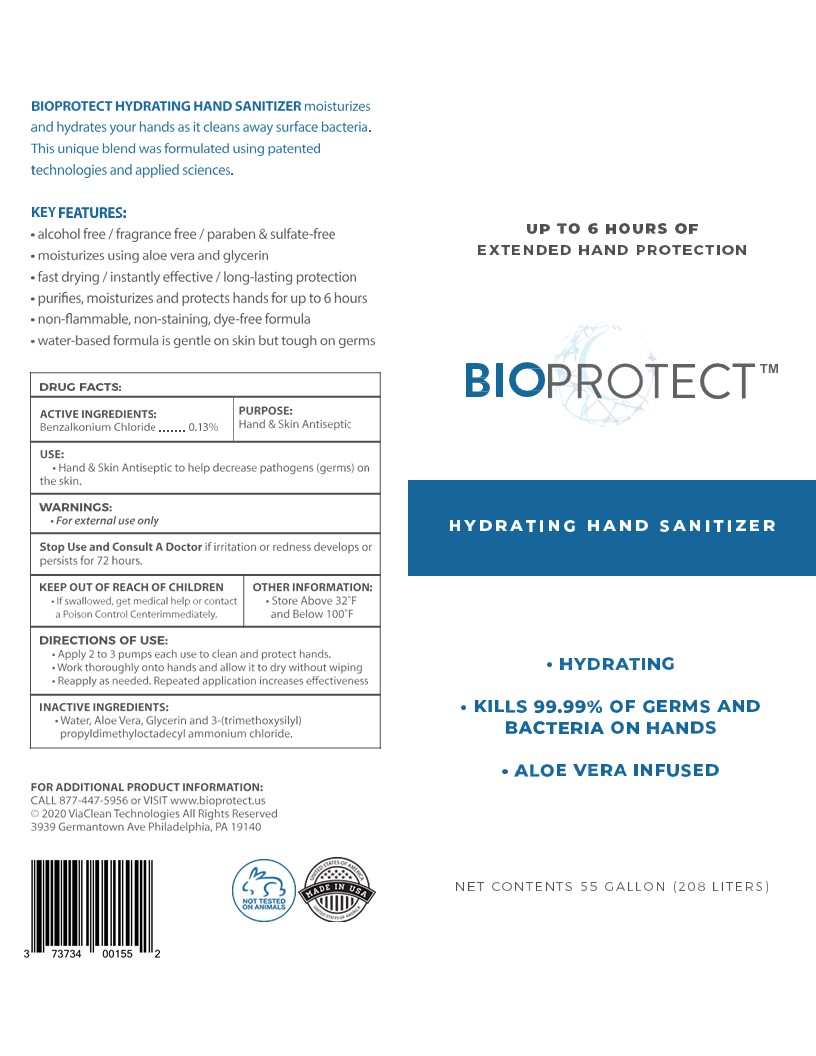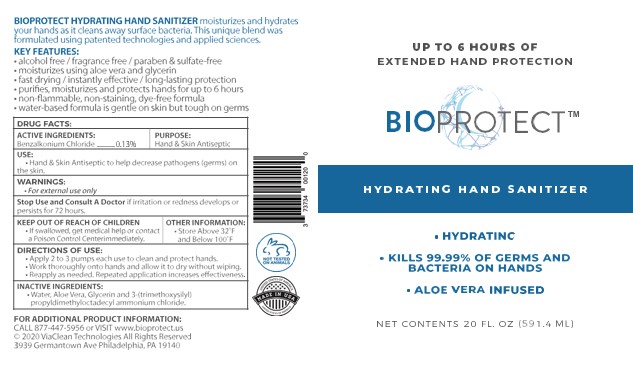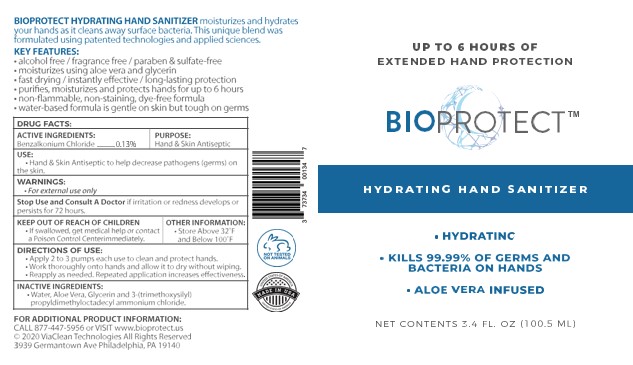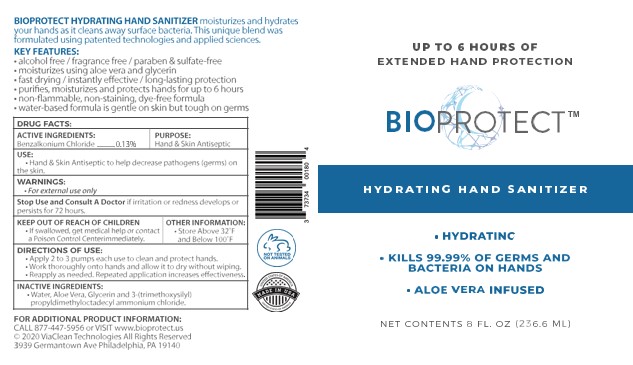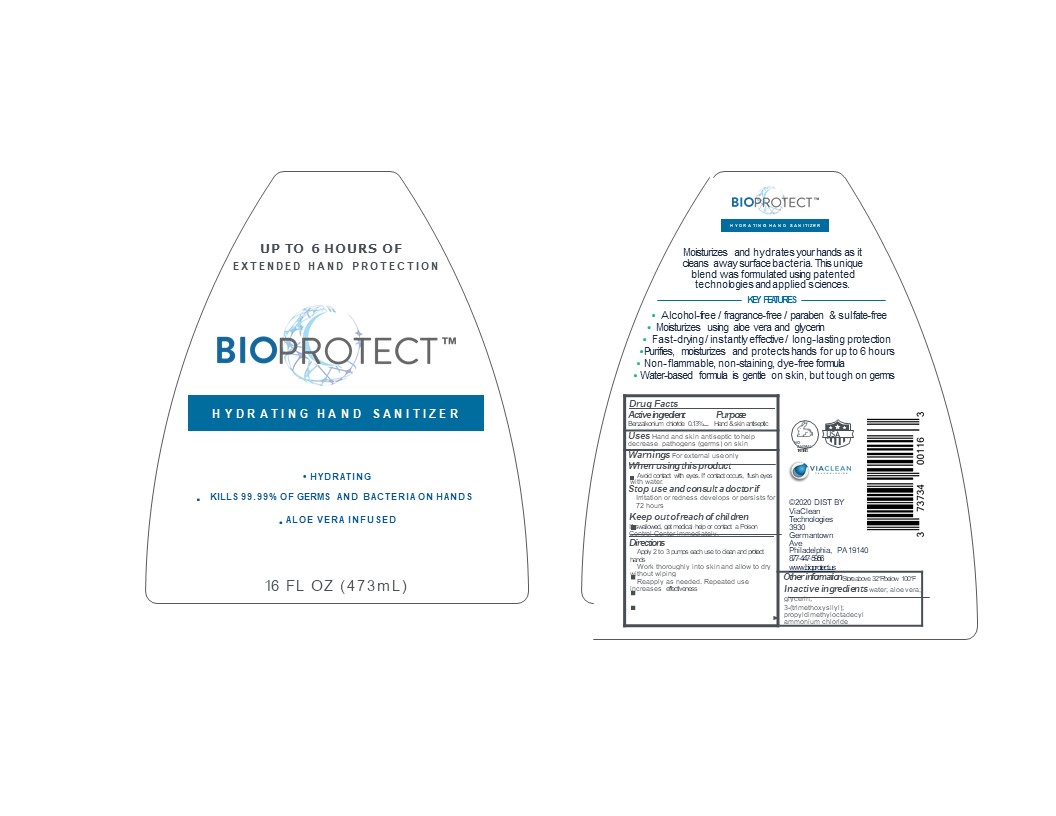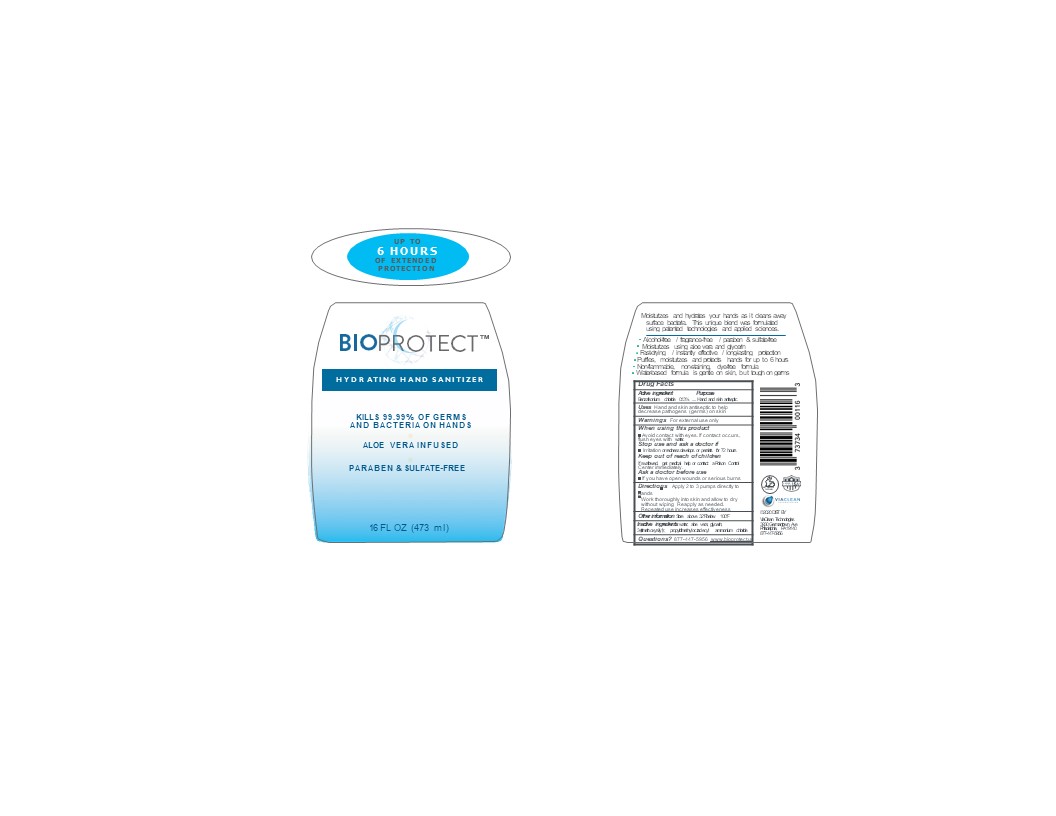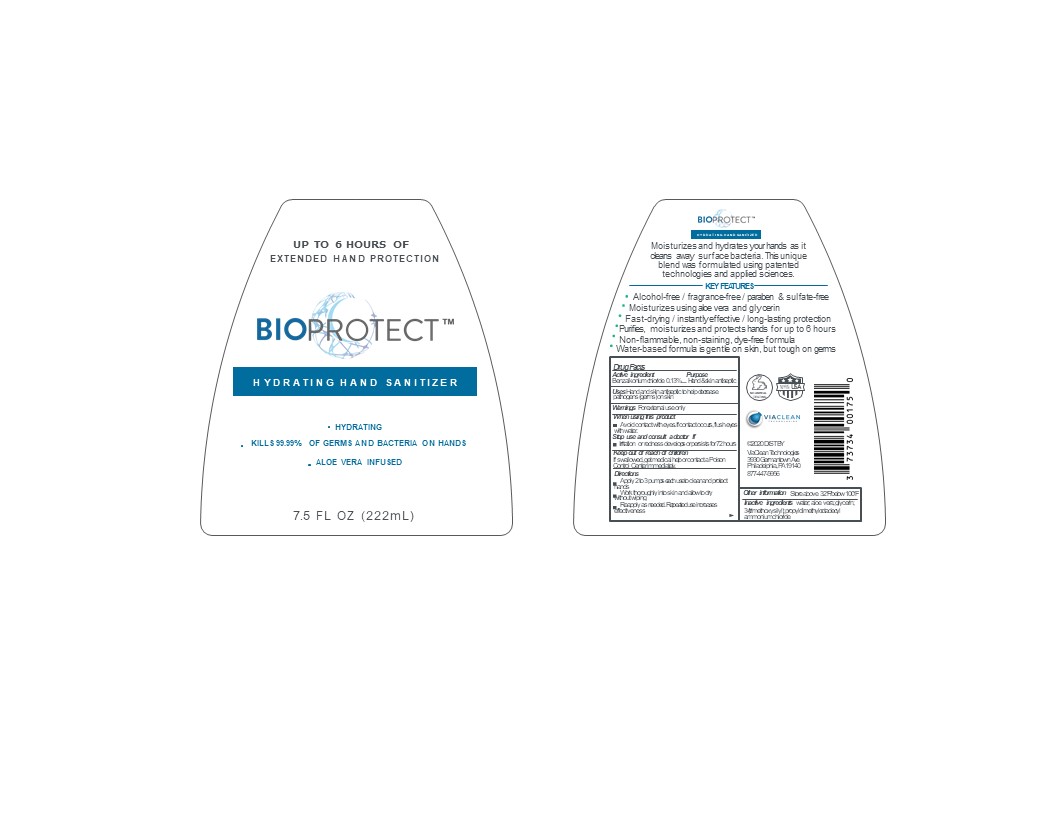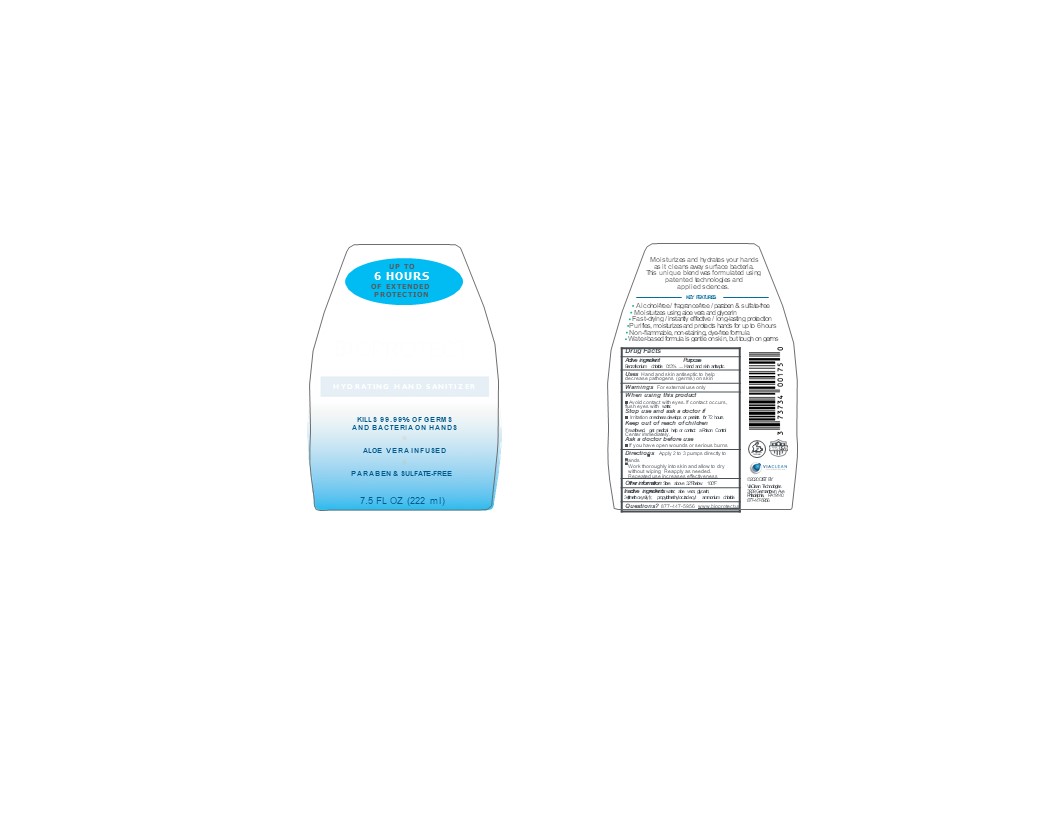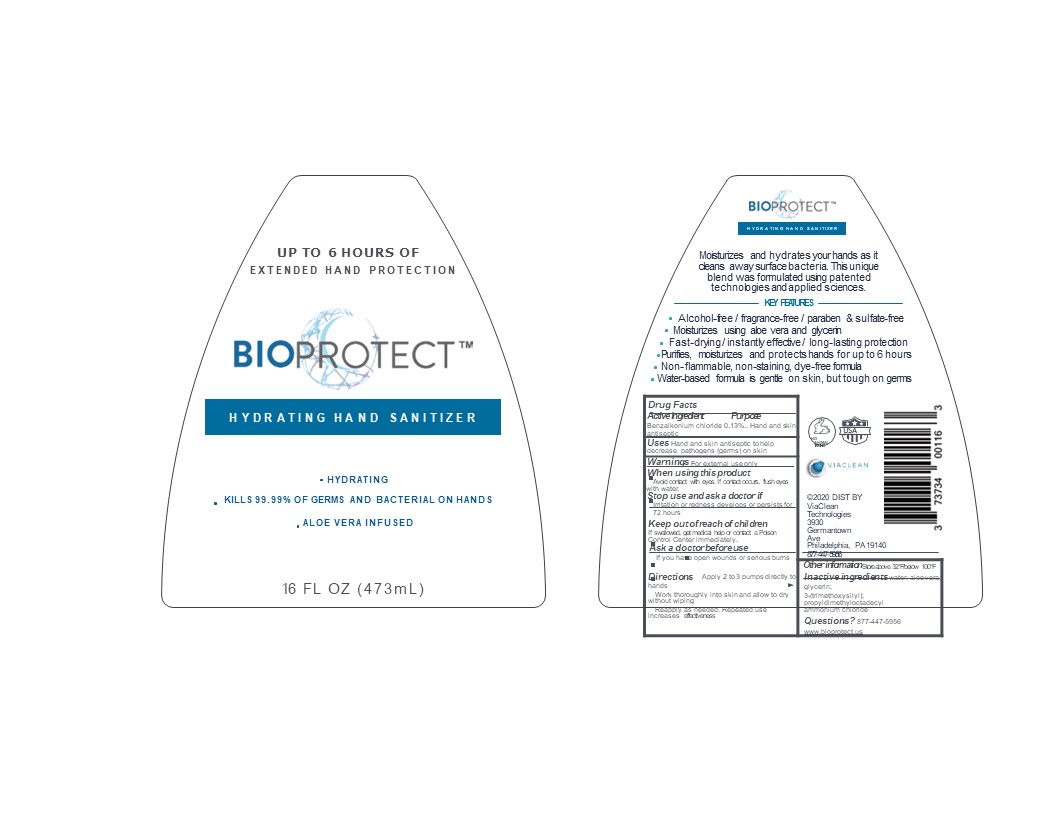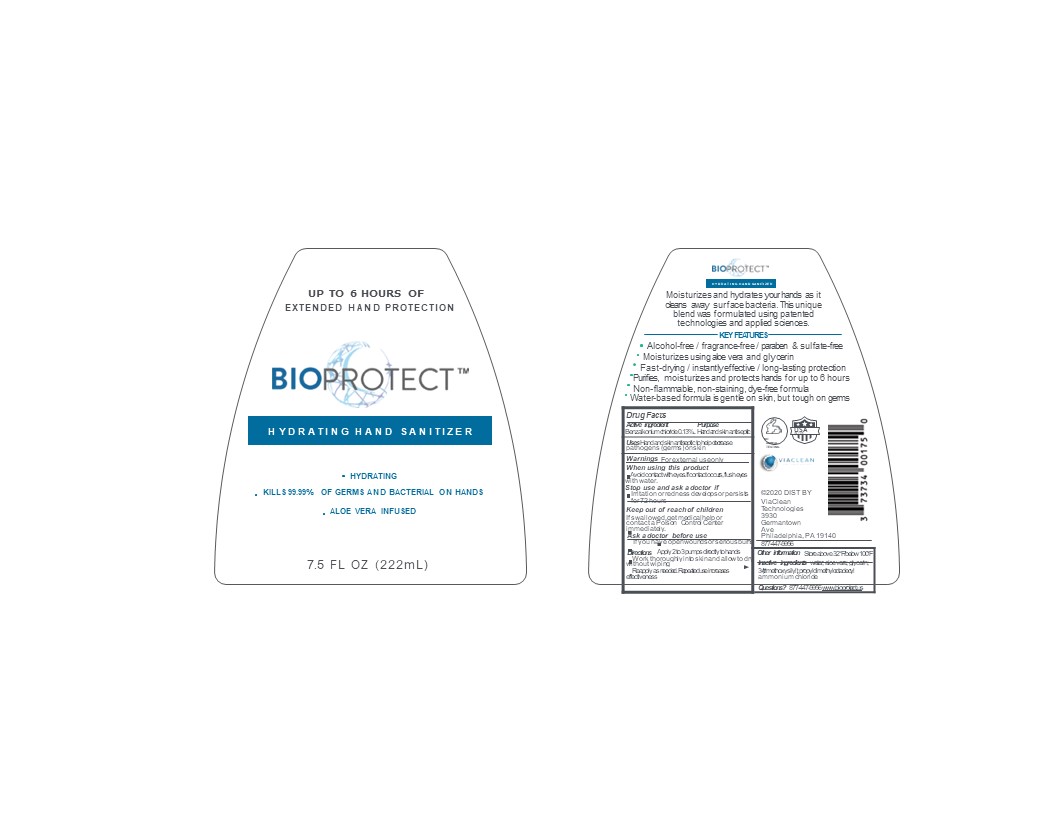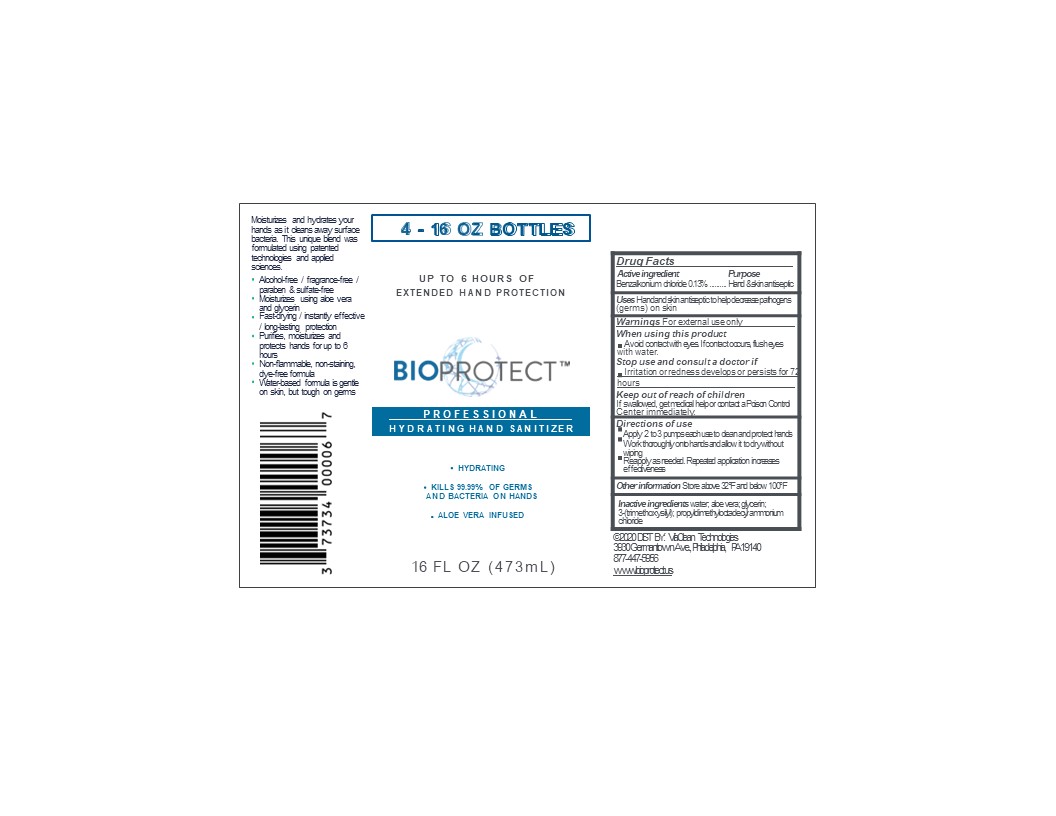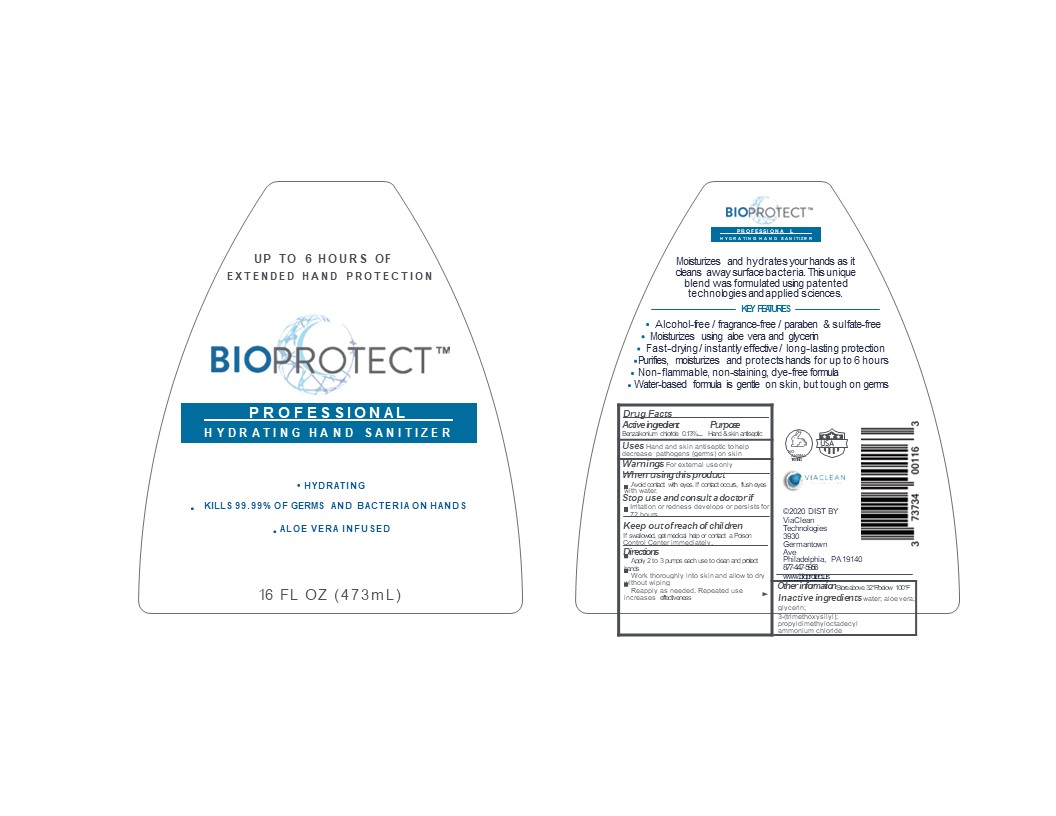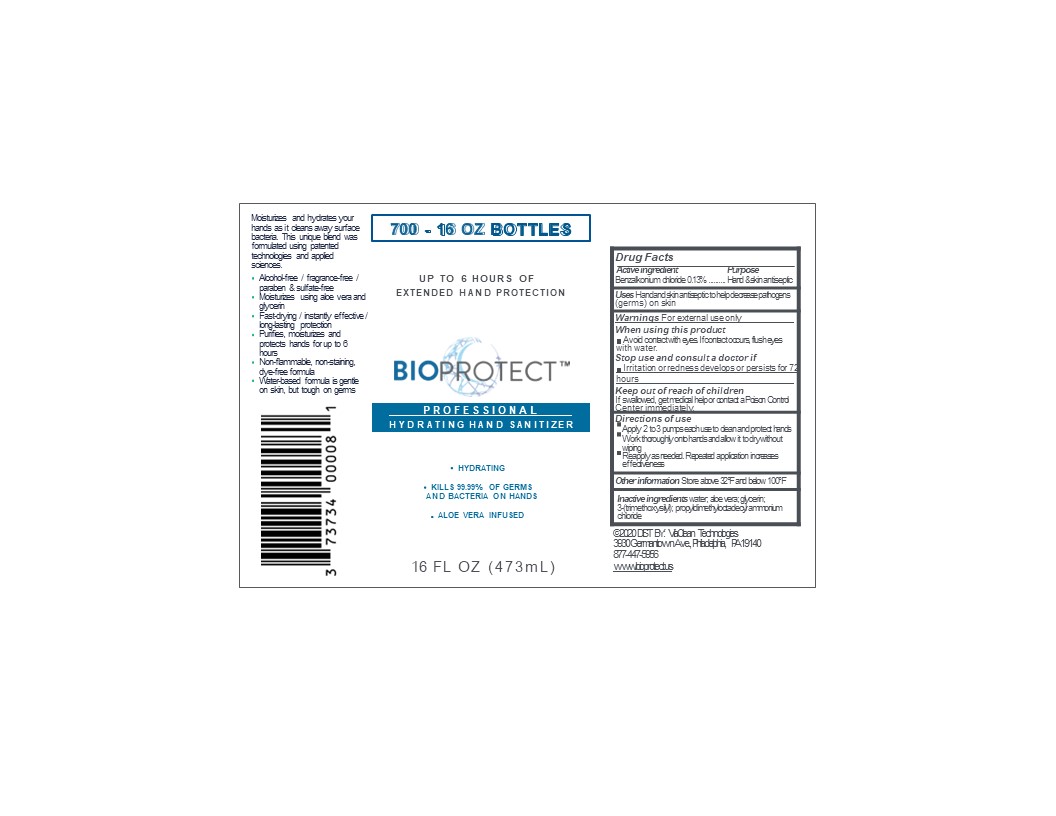 DRUG LABEL: BIOPROTECT Hand Sanitizer
NDC: 73734-001 | Form: LIQUID
Manufacturer: ViaClean Technologies, LLC
Category: otc | Type: HUMAN OTC DRUG LABEL
Date: 20220803

ACTIVE INGREDIENTS: BENZALKONIUM CHLORIDE 0.13 g/100 mL
INACTIVE INGREDIENTS: DIMETHYLOCTADECYL(3-(TRIMETHOXYSILYL)PROPYL)AMMONIUM CHLORIDE; WATER; ALOE; GLYCERIN

Drug Facts

Active ingredient

Benzalkonium Chloride 0.13%

Purpose

Hand and skin Antiseptic

Uses

Hand and Skin Antiseptic to help decrease pathogens (germs) on the skin

Warnings

For external use only.

Do not use

- If you are allergic to any of our ingredients.
- In your eyes, mouth, or eyes.
- If eye contact occurs, flush eyes with water.

Ask a doctor before use if you have

- open wounds.
- serious burns.

Stop use and ask doctor if

- redness or skin irritation develop after use, and persists for more than 72 hours.

Keep out of reach of children

- Children should be supervised when using this product.

Directions

Apply 2 to 3 pumps of BIOPROTECT HYDRATING HAND PURIFIER each use to clean and protect hands. Work thoroughly on to hands and allow to dry without wiping. Reapply as needed. Repeated application increases effectiveness.

INACTIVE INGREDIENT

Water, Aloe, Glycerin, 3-(trimethoxysilyl) propyldimethyloctadecyl ammonium chloride

Questions?

Call: 1-877-447-5953 or email at info@viacleantechnologies.com

PACKAGE LABEL

BIOPROTECT

Hydrating hand sanitizer

Extended hand protection

Aloe Vera infused

Alcohol free/ fragrance free/ paraben and sulfate-free

Moisturizes using aloe vera and glycerin

Fast drying/instantly effective/ long-lasting protection

Non-flammable, non-staining, dye-free formula

Water-based formula is gentle on skin but tough on germs

Made in USA

(Manufactured and Distributed by)

ViaClean Technologies LLC
3939 Germantown Ave,

Bldg. #2, Suite #2

Philadelphia, PA 19140

For additional product information: call 877-447-5956 or Visit www.bioprotect.us

(c) 2020 ViaClean Technologies All Rights Reserved

XXfl oz (XX mL) NDC 73734-001-XX